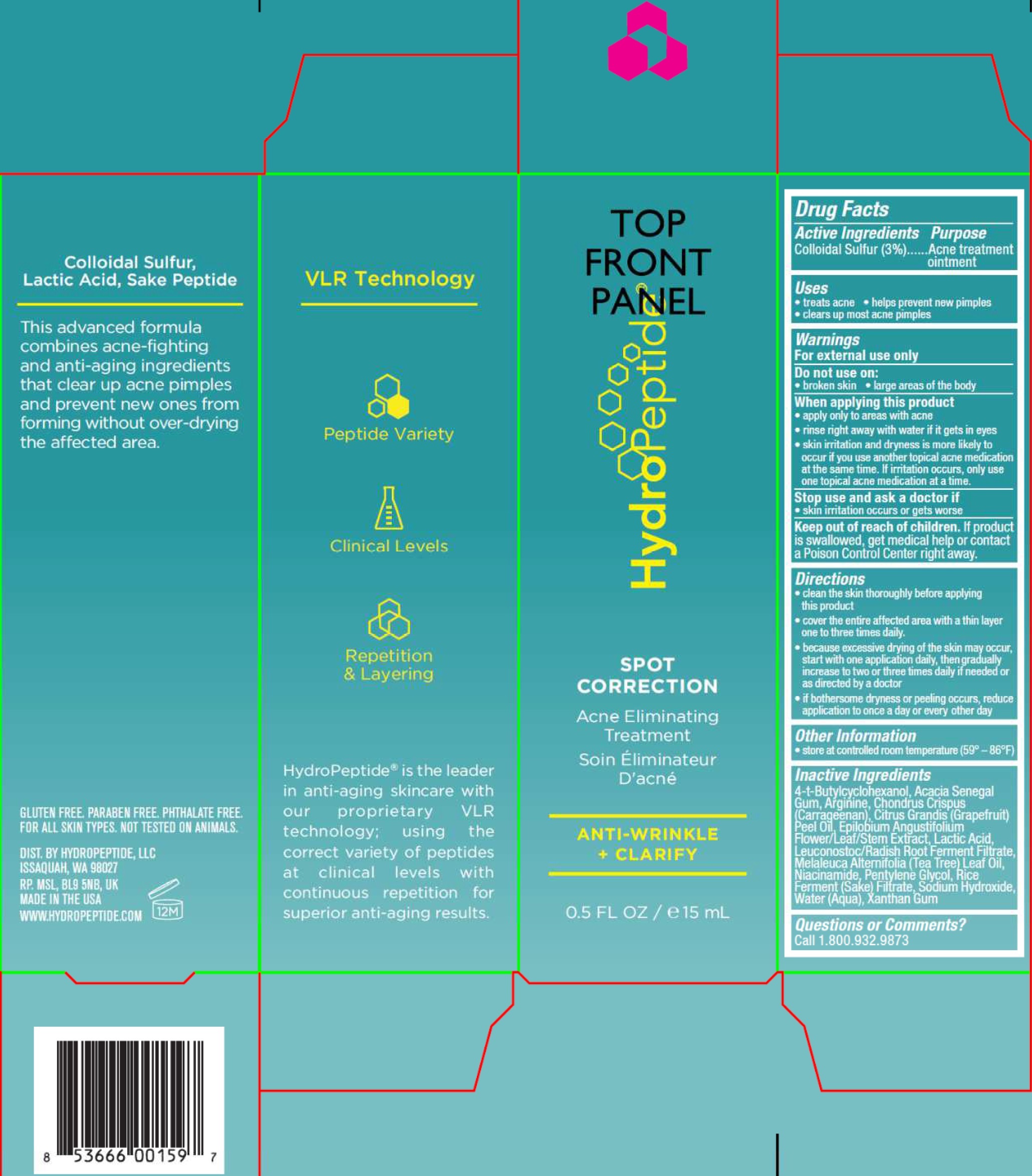 DRUG LABEL: Spot Correction
NDC: 60934-002 | Form: CREAM
Manufacturer: HydroPeptide LLC
Category: otc | Type: HUMAN OTC DRUG LABEL
Date: 20231209

ACTIVE INGREDIENTS: SULFUR 30 mg/1 mL
INACTIVE INGREDIENTS: 4-TERT-BUTYLCYCLOHEXANOL; ACACIA; ARGININE; CHONDRUS CRISPUS CARRAGEENAN; CITRUS MAXIMA FRUIT RIND OIL; EPILOBIUM ANGUSTIFOLIUM FLOWERING TOP; LACTIC ACID; LEUCONOSTOC/RADISH ROOT FERMENT FILTRATE; TEA TREE OIL; NIACINAMIDE; PENTYLENE GLYCOL; SODIUM HYDROXIDE; WATER; XANTHAN GUM

Spot Correction

Active Ingredients

Colloidal Sulfur (3%)

Purpose

Acne treatment ointment

Uses

- treats acne
- helps prevent new pimples
- clears up most acne pimples

Warnings

For external use only

Do not use on:

- broken skin
- large areas of the body

When applying this product

- apply only to areas with acne
- rinse right away with water if it gets in eyes
- skin irritation and dryness is more likely to occur if you use another topical acne medication at the same time. If irritation occurs, only use one topical acne medication at a time.

Stop use and ask a doctor if

- skin irritation occurs or gets worse

Keep out of reach of children.

If product is swallowed, get medical help or contact a Poison Control Center right away.

Directions

- clean the skin thoroughly before applying this product
- cover the entire affected area with a thin layer one to three times daily.
- because excessive drying of the skin may occur, start with one application daily, then gradually increase to two or three times daily if needed or as directed by a doctor
- if bothersome dryness or peeling occurs, reduce application to once a day or every other day

Other Information

- store at controlled room temperature (59° - 86°F)

Inactive Ingredients

4-t-Butylcyclohexanol, Acacia Senegal Gum, Arginine, Chondrus Crispus (Carrageenan), Citrus Grandis (Grapefruit) Peel Oil, Epilobium Angustifolium Flower/Leaf/Stem Extract, Lactic Acid, Leuconostoc/Radish Root Ferment Filtrate, Melaleuca Alternifolia (Tea Tree) Leaf Oil, Niacinamide, Pentylene Glycol, Rice Ferment (Sake) Filtrate, Sodium Hydroxide, Water (Aqua), Xanthan Gum

Questions or Comments?

Call 1.800.932.9873